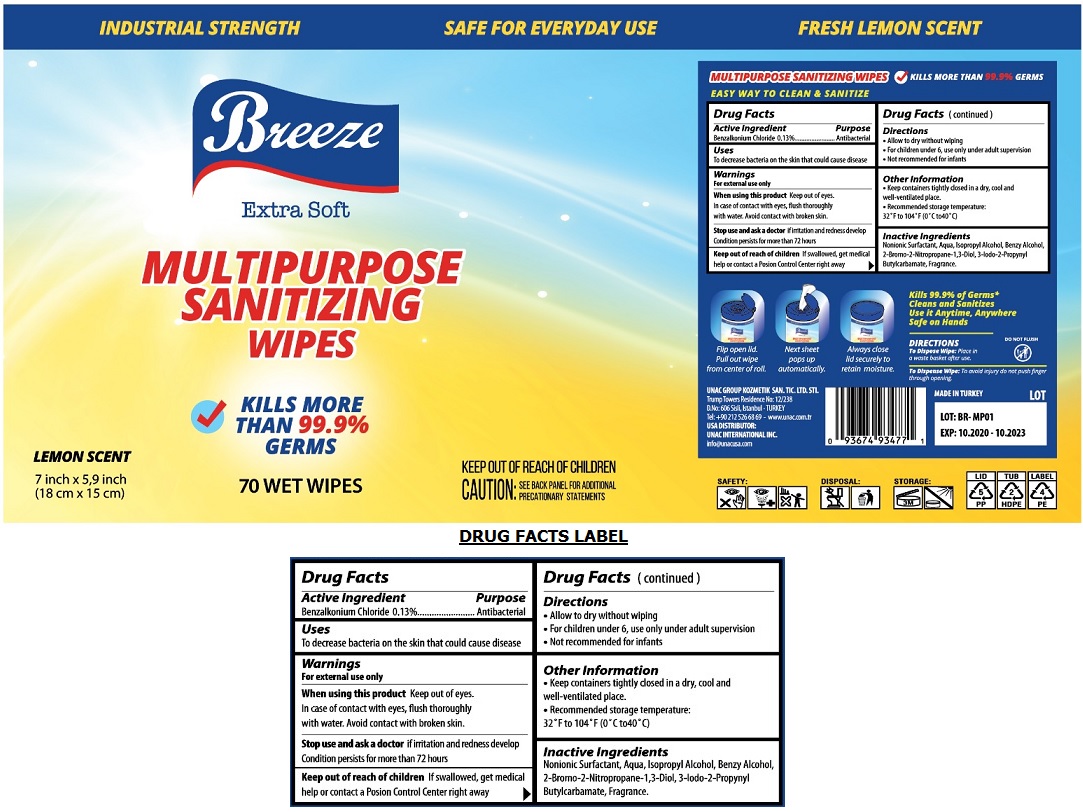 DRUG LABEL: BREEZE MULTIPURPOSE SANITIZING WIPES
NDC: 74955-029 | Form: CLOTH
Manufacturer: COSMOLIVE KOZMETIK SANAYI VE TICARET ANONIM SIRKETI
Category: otc | Type: HUMAN OTC DRUG LABEL
Date: 20201124

ACTIVE INGREDIENTS: BENZALKONIUM CHLORIDE 0.13 g/100 g
INACTIVE INGREDIENTS: BERACTANT; WATER; ISOPROPYL ALCOHOL; BENZYL ALCOHOL; BRONOPOL; 3-IODO-2-PROPYNOL; BUTYL CARBAMATE

Breeze MULTIPURPOSE SANITIZING WIPES

Active Ingredient

Benzalkonium Chloride 0.13%

Purpose

Antibacterial

Uses

To decrease bacteria on the skin that could cause disease

Warnings

For external use only

When using this product Keep out of eyes. In case of contact with eyes, flush thoroughly with water. Avoid contact with broken skin.

Stop use and ask a doctor if irritation and redness develop

Condition persists for more than 72 hours

Keep out of reach of children If swallowed, get medical help or contact a Poison Control Center right away.

Directions

• Allow to dry without wiping

• For children under 6, use only under adult supervision

• Not recommended for infants

Other Information

• Keep containers tightly closed in a dry, cool and well-ventilated place.

• Recommended storage temperature: 32° F to 104° F (0° C to40°C)

Inactive Ingredients

Nonionic Surfactant, Aqua, Isopropyl Alcohol, Benzyl Alcohol, 2-Bromo-2-Nitropropane-1, 3-Diol, 3-lodo-2-Propynyl, Butylcarbamate, Fragrance.

Extra Soft

√ KILLS MORE THAN 99.9% GERMS

INDUSTRIAL STRENGTH

SAFE FOR EVERYDAY USE

FRESH LEMON SCENT

KEEP OUT OF REACH OF CHILDREN

CAUTION: SEE BACK PANEL FOR ADDITIONAL PRECAUTIONARY STATEMENTS

EASY WAY TO CLEAN & SANITIZE

Flip open lid. Pull out wipe from center of roll.

Next sheet pops up automatically.

Always close lid securely to retain moisture.

Kills 99.9% of Germs*

Cleans and Sanitizes

Use it Anytime, Anywhere

Safe on hands

DIRECTIONS

To Dispose Wipe: Place in a waste basket after use.

DO NOT FLUSH

To Dispense Wipe: To avoid injury do not push finger through opening

UNAC GROUP KOZMETIK SAN. TIC. LTD. STI

Trump Towers Residence No: 12/238

D.No:606 Sisli, Istanbul - TURKEY

Tel: +90 212 526 68 69 - www.unac.com.tr

USA DISTRIBUTOR:

UNAC INTERNATIONAL INC.

info@unacusa.com

MADE IN TURKEY